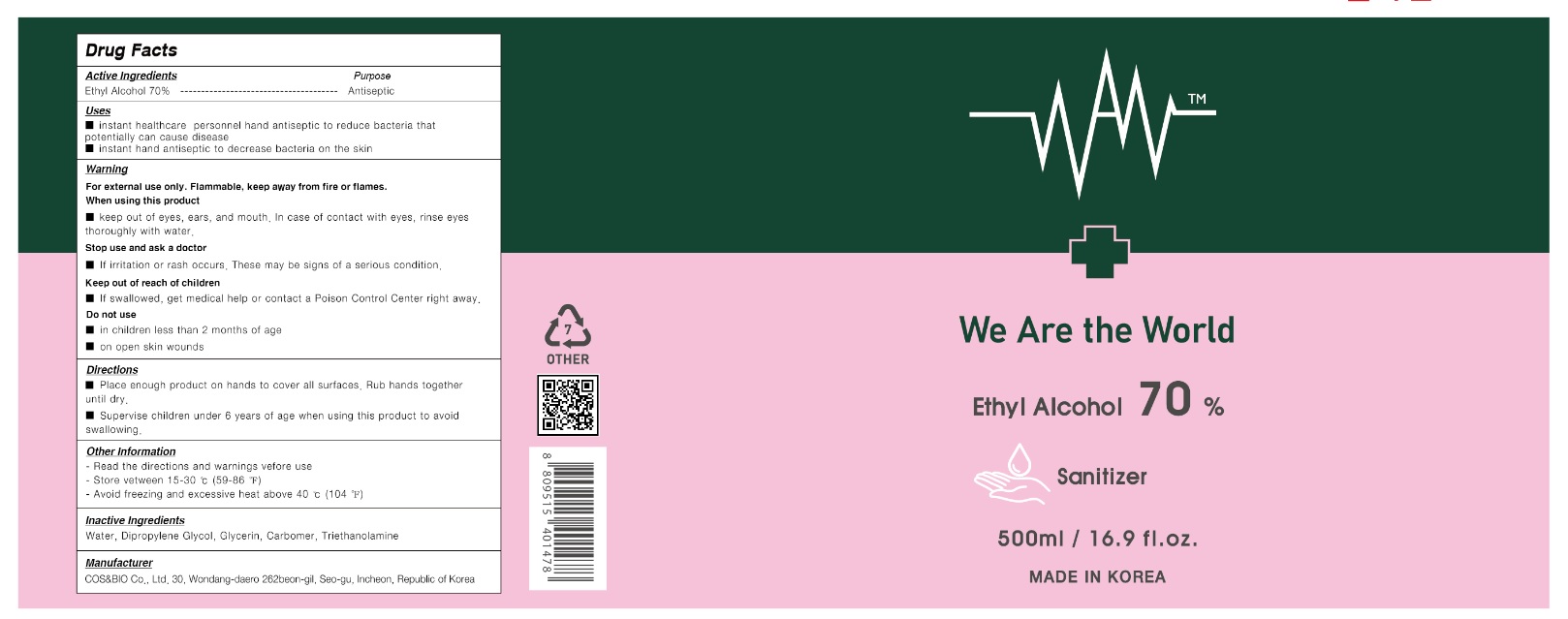 DRUG LABEL: We Are The World Sanitizer (Ethyl alcohol 70%)
NDC: 76770-7500 | Form: GEL
Manufacturer: COS&BIO Co Ltd
Category: otc | Type: HUMAN OTC DRUG LABEL
Date: 20200604

ACTIVE INGREDIENTS: ALCOHOL 350 mL/500 mL
INACTIVE INGREDIENTS: GLYCERIN; CARBOMER HOMOPOLYMER, UNSPECIFIED TYPE; WATER; TROLAMINE; DIPROPYLENE GLYCOL

[COS&BIO Co Ltd] We Are The World Sanitizer (Ethyl alcohol 70%) 500 mL | Bottle+Pump | 76770-7500-1